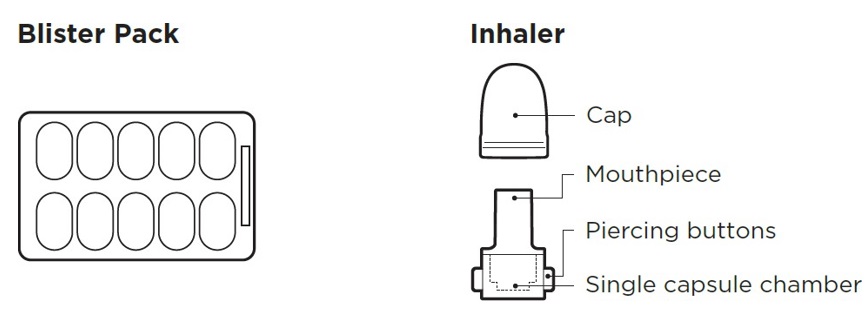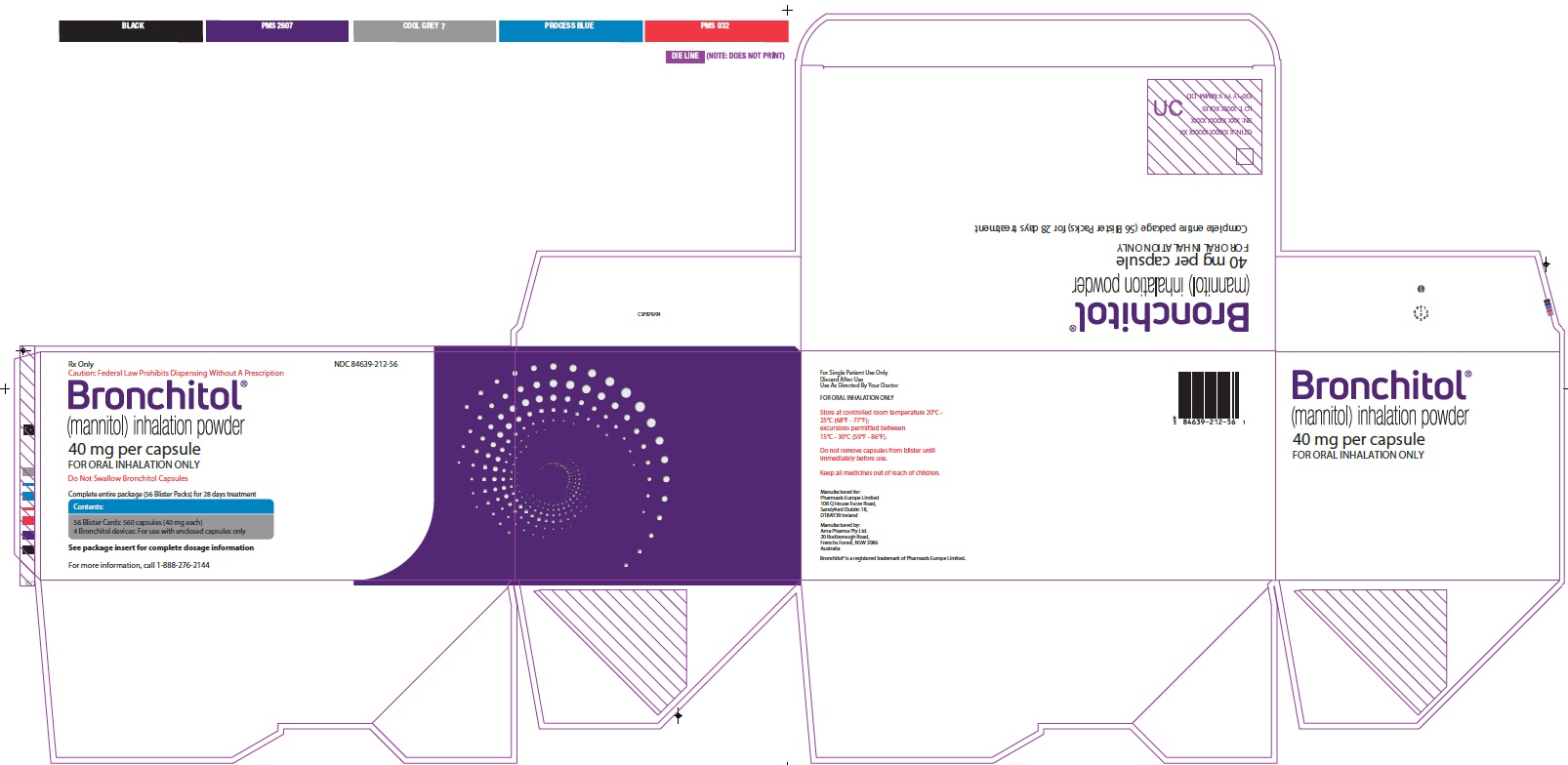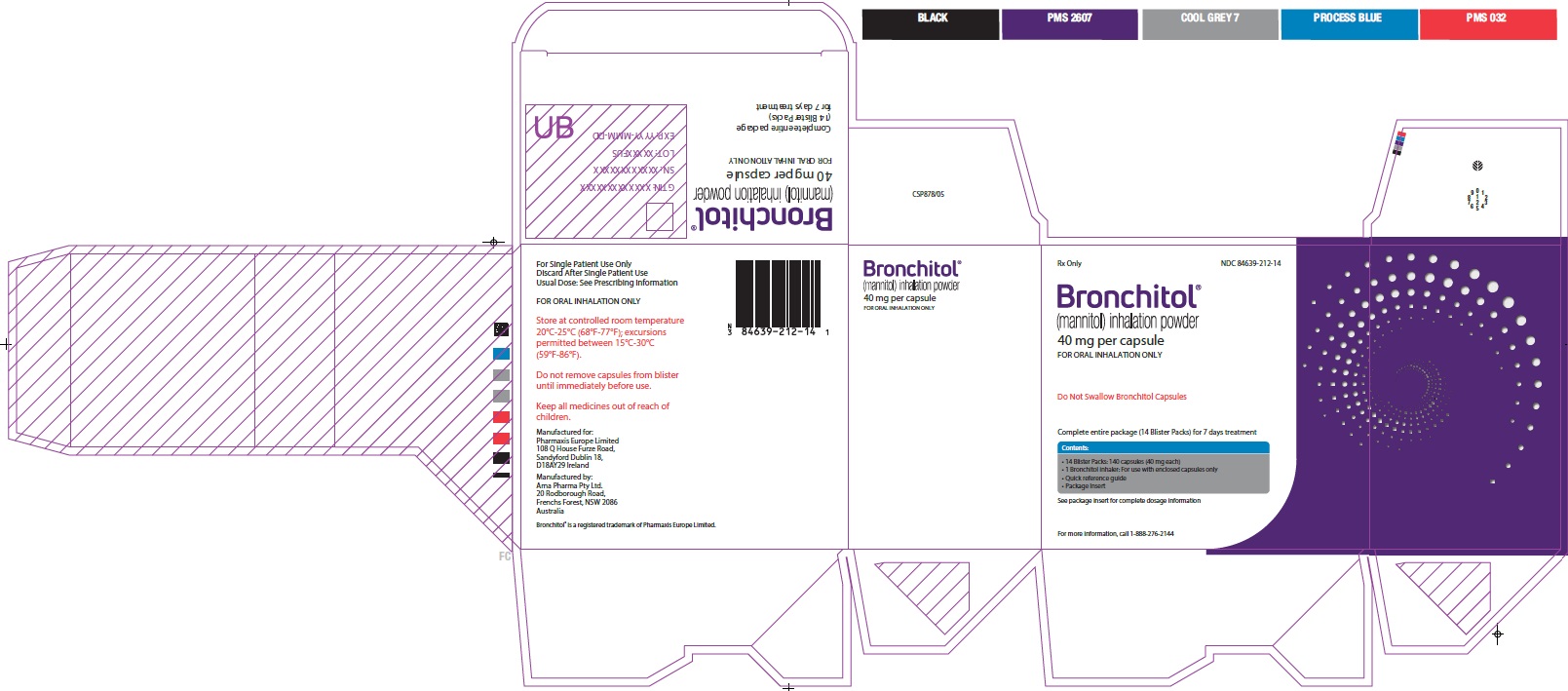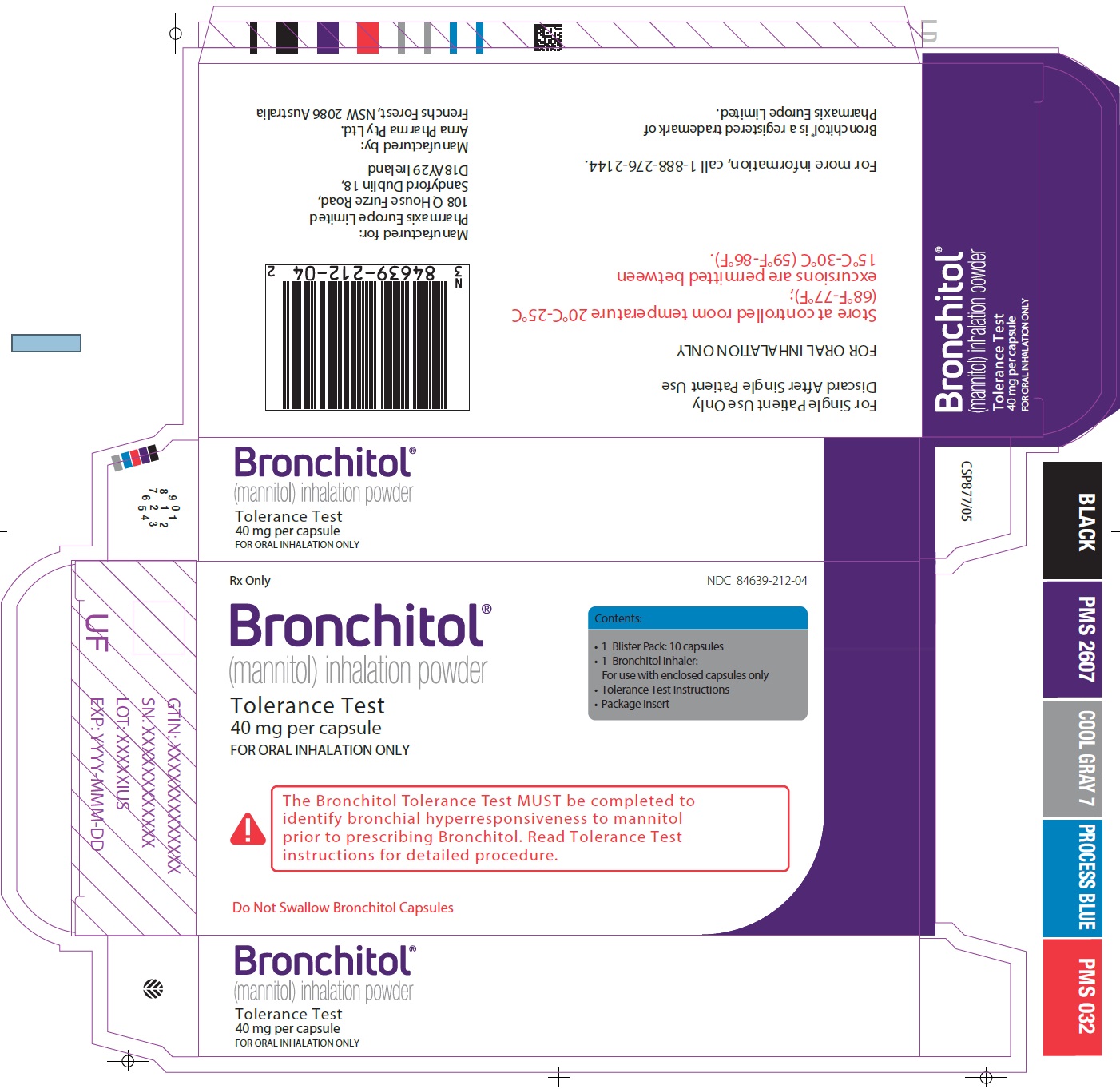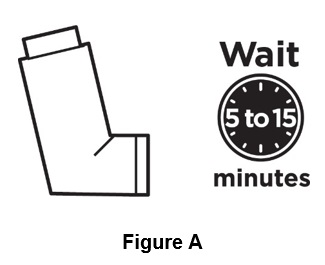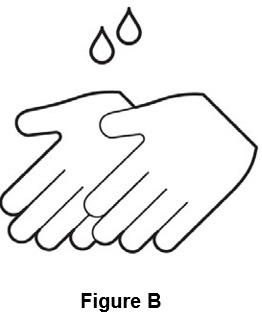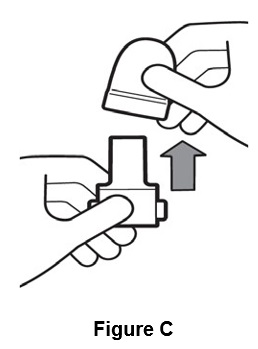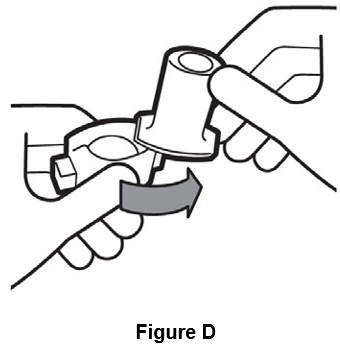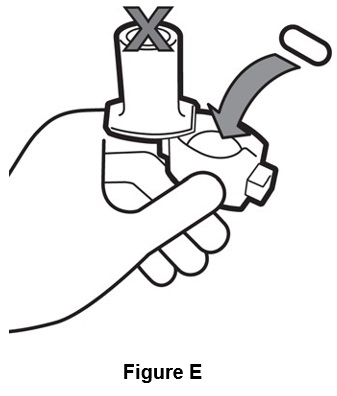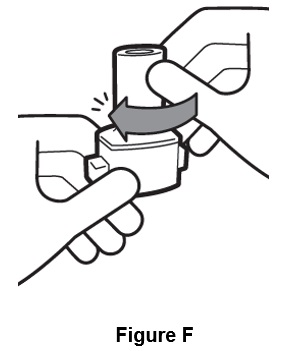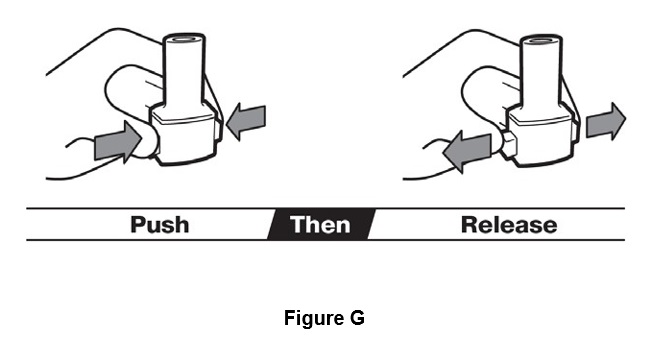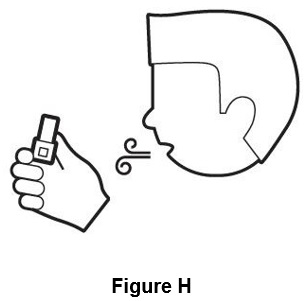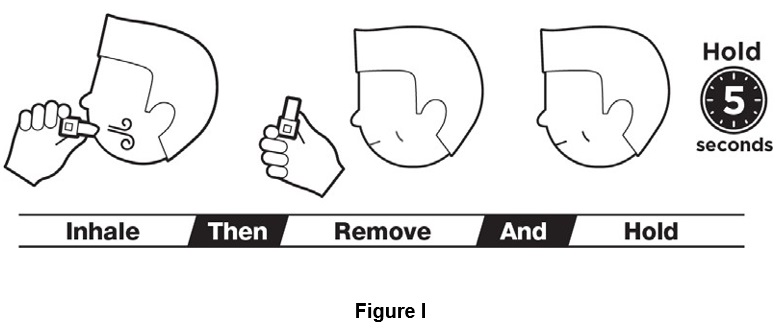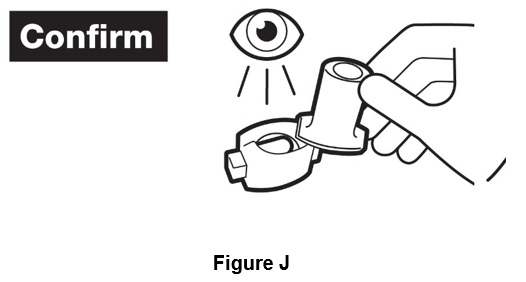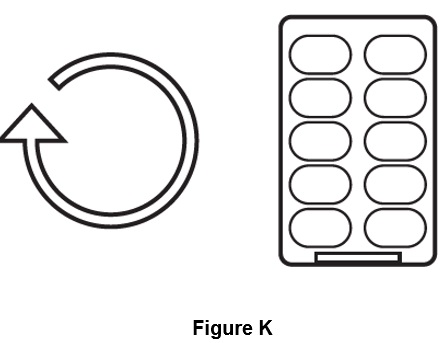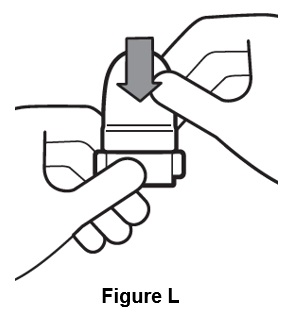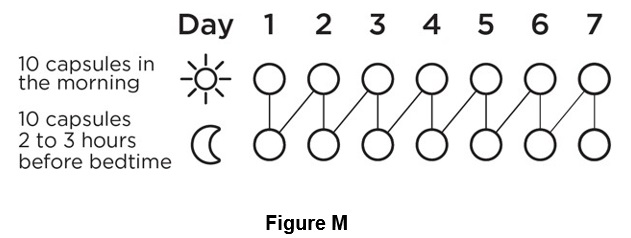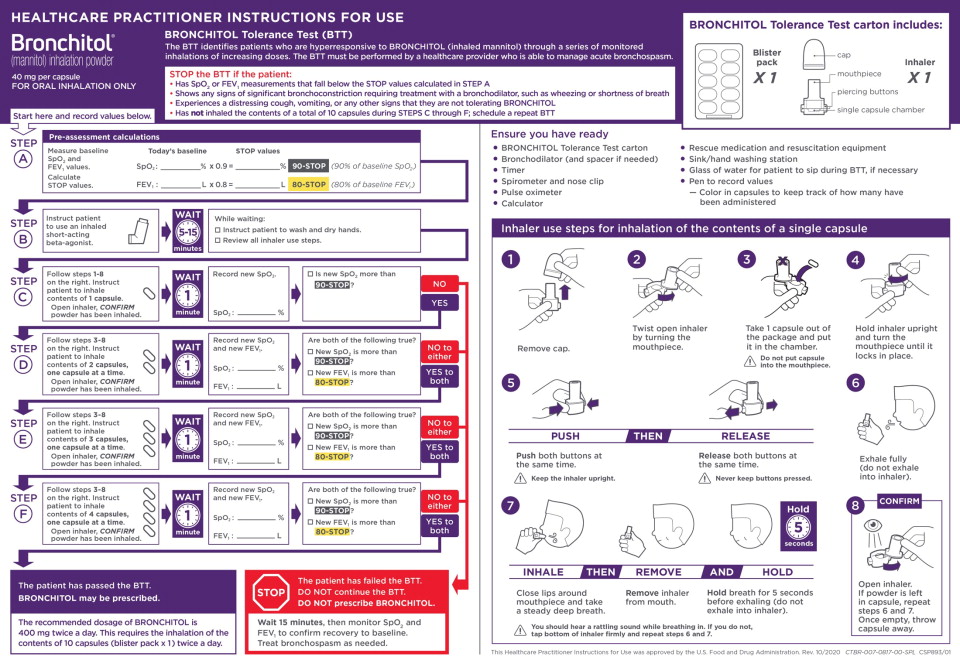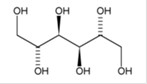 DRUG LABEL: BRONCHITOL
NDC: 84639-212 | Form: CAPSULE
Manufacturer: Arna Pharma Pty Ltd
Category: prescription | Type: HUMAN PRESCRIPTION DRUG LABEL
Date: 20240903

ACTIVE INGREDIENTS: MANNITOL 40 mg/10 1

HIGHLIGHTS OF PRESCRIBING INFORMATION

These highlights do not include all the information needed to use BRONCHITOL safely and effectively.
See full prescribing information for BRONCHITOL.
BRONCHITOL® (mannitol) inhalation powder, for oral inhalation use
Initial U.S. Approval: 1964

1 INDICATIONS & USAGE SECTION

BRONCHITOL is a sugar alcohol indicated as add-on maintenance therapy to improve pulmonary function in adult patients 18 years of age and older with cystic fibrosis. Use BRONCHITOL only in adults who have passed the BRONCHITOL Tolerance Test. (1)

2 DOSAGE AND ADMINISTRATION

- For Oral Inhalation Only. (2.1)
- The BRONCHITOL Tolerance Test is administered to identify patients who are appropriate for inhaled mannitol use. (2.1)
- Treatment of cystic fibrosis: 400 mg of BRONCHITOL (10 capsules) twice a day by oral inhalation, in the morning and evening, with the later dose taken 2-3 hours before bedtime. (2.2)

4 CONTRAINDICATIONS

- Hypersensitivity to mannitol or to any of the capsule components. (4)
- Failure to pass the BRONCHITOL Tolerance Test. (4)

5 WARNINGS AND PRECAUTIONS

- BRONCHITOL can cause bronchospasm, which can be severe in susceptible patients. Because of the risk of bronchospasm, prior to prescribing BRONCHITOL, perform the BRONCHITOL tolerance test (BTT). The BTT must be administered under the supervision of a healthcare practitioner who can treat severe bronchospasm. Do not prescribe BRONCHITOL if the patient fails the BTT. Patients who pass the BTT may experience bronchospasm with maintenance use of BRONCHITOL. Advise patients to premedicate with an inhaled short- acting bronchodilator prior to each administration of BRONCHITOL. If bronchospasm occurs, immediately discontinue BRONCHITOL. Treat bronchospasm with an inhaled short-acting bronchodilator. (2.1, 5.1)
- Hemoptysis can occur with BRONCHITOL use. Monitor patients with history of episodes of hemoptysis. If hemoptysis occurs, discontinue use of BRONCHITOL (5.2)

6 ADVERSE REACTIONS

Most common adverse reactions (≥3%) include cough, hemoptysis, oropharyngeal pain, vomiting, bacteria sputum identified, pyrexia, and arthralgia. (6.1)

To report SUSPECTED ADVERSE REACTIONS, contact Pharmaxis Europe Limited at 1-888-276-0618 or FDA at 1-800-FDA-1088 or

www.fda.gov/medwatch.

See 17 for PATIENT COUNSELING INFORMATION and

FDA-approved patient labeling.

Revised: 06/2024

FULL PRESCRIBING INFORMATION

1 INDICATIONS & USAGE SECTION

BRONCHITOL is indicated as add-on maintenance therapy to improve pulmonary function in adult patients 18 years and older with Cystic Fibrosis. Use BRONCHITOL only for adults who have passed the BRONCHITOL Tolerance Test [see Dosage and Administration (2.1)].

2 DOSAGE AND ADMINISTRATION

2.1 Required Testing and Evaluation Prior to Prescribing BRONCHITOL (BRONCHITOL Tolerance Test)

Prior to prescribing BRONCHITOL for treatment of cystic fibrosis, the BRONCHITOL Tolerance Test (BTT) must be administered and performed under the supervision of a healthcare practitioner who is able to manage acute bronchospasm, to identify patients who are suitable candidates for BRONCHITOL maintenance therapy.

- Perform BTT to identify patients who experience bronchospasm, a decrease in FEV1, or a decrease in oxygen saturation with administration of BRONCHITOL. If a patient experiences any of these events during the BTT, the patient has failed the BTT. Do not prescribe BRONCHITOL. If a patient does not experience any of these events during BTT, the patient has passed the BTT and is a candidate for BRONCHITOL therapy.

- Ensure that rescue medication and resuscitation equipment are available for immediate use during the BTT.
- Do not perform the BTT if the patient is considered clinically unstable.

See the BTT Healthcare Practitioner (HCP) Instructions for Use (IFU) for complete instructions and to avoid medication errors
associated with BTT dosing and procedures.

Do not use BRONCHITOL add-on maintenance therapy in patients who fail the BTT [see Contraindications (4)].

2.2 Recommended Dosage for Treatment of Cystic Fibrosis

For patients who have passed the BTT, the recommended dosage of BRONCHITOL is 400 mg twice a day by oral inhalation (the contents of 10 capsules administered individually) via the inhaler [see Dosage and Administration (2.1)].

A short-acting bronchodilator should be administered by oral inhalation, 5-15 minutes before every dose of BRONCHITOL.

BRONCHITOL should be taken once in the morning and once in the evening, with the later dose taken at least 2-3 hours before
bedtime.

2.3 Use and Maintenance of Inhaler

Instruct patients on safe hygiene practices (clean and dry hands thoroughly) and correct inhaler use, including loading of capsules and proper inhalation technique per the Patient Instructions for Use.

The BRONCHITOL inhaler should be discarded and replaced after 7 days of use. If the inhaler does need to be washed, the patient should allow the inhaler to thoroughly air dry before next use.

3 DOSAGE FORMS AND STRENGTHS

Inhalation powder: 40 mg mannitol per capsule; clear, colorless hard gelatin capsule imprinted with “PXS 40 mg”

4 CONTRAINDICATIONS

BRONCHITOL is contraindicated in the following conditions:

- Hypersensitivity to mannitol or to any of the capsule components
- Failure to pass the BRONCHITOL Tolerance Test (BTT)

5 WARNINGS AND PRECAUTIONS

5.1 Bronchospasm

BRONCHITOL Tolerance Test
BRONCHITOL can cause bronchospasm, which can be severe in susceptible individuals. Because of the risk of bronchospasm, prior to prescribing BRONCHITOL, perform the BRONCHITOL Tolerance Test (BTT), to identify patients who are appropriate for maintenance treatment with BRONCHITOL. The BTT must be administered under the supervision of a healthcare practitioner who can treat severe bronchospasm. In clinical trials, 896 adult patients with cystic fibrosis underwent the BTT and 72 patients (8%) failed or did not complete the BTT. Do not prescribe BRONCHITOL if the patient fails the BTT.

Maintenance Therapy
Bronchospasm may occur during inhalation of BRONCHITOL, even in patients who have passed the BTT. An inhaled short-acting bronchodilator must be administered 5-15 minutes before administration of each dose during maintenance therapy. In clinical studies, bronchospasm or bronchial hyperreactivity was reported in 4 of 414 adult patients (1.0%) receiving BRONCHITOL as maintenance therapy and in 2 of 347 adult patients (0.6%) receiving control (50 mg inhaled mannitol), even though these patients had passed the BTT. If bronchospasm occurs following dosing of BRONCHITOL, it should immediately be discontinued and treated with an inhaled short-acting bronchodilator or as medically appropriate.

5.2 Hemoptysis

Hemoptysis may occur with BRONCHITOL use. Hemoptysis was reported in 43 (10.4%) adult patients receiving BRONCHITOL and in 33 (9.5%) adult patients receiving control (50 mg inhaled mannitol) during clinical studies. In patients aged 6 years to 17 years, hemoptysis was reported in 12 of 154 (7.8%) patients who received BRONCHITOL and in 2 of 105 (1.9%) patients who received control. BRONCHITOL has not been studied in patients with a history of episodes of significant hemoptysis (volume greater than 60 mL) in the previous 3 months. BRONCHITOL should be discontinued in the event of hemoptysis. BRONCHITOL is not indicated for use in children and adolescents.

6 ADVERSE REACTIONS

The following clinically significant adverse reactions are described elsewhere in the labeling:

Bronchospasm [see Warnings and Precautions (5.1)]
Hemoptysis [see Warnings and Precautions (5.2)]

7 DRUG INTERACTIONS

No formal drug interaction studies have been conducted with mannitol, the active ingredient in BRONCHITOL.

8 USE IN SPECIFIC POPULATIONS

8.1 Pregnancy

Risk Summary

There are no adequate and well-controlled studies of BRONCHITOL in pregnant women. The available data on BRONCHITOL use in pregnant women are not sufficient to inform any drug-associated risks for major birth defects and miscarriage. Based on animal reproduction studies, no evidence of structural alterations was observed when mannitol was administered to pregnant rats and mice during organogenesis at doses up to approximately 20 and 10 times, respectively, the maximum recommended daily inhalation dose (MRDID) in humans [ see Data]. There are risks to the mother associated with cystic fibrosis in pregnancy [see Clinial Considerations]. BRONCHITOL should be used during pregnancy only if the potential benefit justifies the potential risk to the mother and fetus.

The estimated background risk of major birth defects and miscarriage for the indicated population is unknown. All pregnancies have a background risk of birth defect, loss, or other adverse outcomes. In the United States general population, the estimated background risk of major birth defects and miscarriage in clinically recognized pregnancies is 2 to 4% and 15 to 20%, respectively.

Clinical Considerations

Disease-Associated Maternal and/or Embryo/Fetal Risk

Cystic fibrosis may increase the risk for preterm delivery. Data

Animal Data

In animal reproduction studies, oral administration of mannitol to pregnant rats and mice during the period of organogenesis did not cause fetal structural alterations. The mannitol dose in rats and mice was approximately 20 and 10 times the maximum recommended human daily inhalation dose (MRDID) in humans, respectively, (on a mg/m^2 basis at maternal doses of 1600 mg/kg/day in both species).

8.2 Lactation

Risk Summary

It is not known whether BRONCHITOL is excreted in human breast milk. The developmental and health benefits of breastfeeding should be considered along with the mother’s clinical need for BRONCHITOL and any potential adverse effects on the breastfed child from BRONCHITOL or from the underlying maternal condition.

8.4 Pediatric Use

BRONCHITOL is not indicated for use in children and adolescents. The safety and effectivenss of BRONCHITOL have not been established in pediatric patients for cystic fibrosis. Patients aged 6 years to 17 years were included in two 26- week, double-blind clinical trials (Trials 2 and 3). In these trials, 154 patients under 18 years of age received BRONCHITOL and 105 patients received control (50 mg inhaled mannitol). Hemoptysis was reported in 12 of 154 (7.8%) patients who received BRONCHITOL and in 2 of 105 (1.9%) patients who received control.

8.5 Geriatric Use

Clinical trials of BRONCHITOL did not include sufficient numbers of patients with cystic fibrosis who were 65 years of age and older to allow evaluation of safety and efficacy in this population.

8.6 Hepatic and Renal Impairment

Clinical trials of BRONCHITOL did not include patients with hepatic or renal impairment. No specific dose recommendations for these patient populations are available. However, an increase in systemic exposure of mannitol can be expected in patients with renal impairment based on the kidney being its primary route of elimination.

10 OVERDOSAGE

Susceptible persons may experience bronchoconstriction from an overdosage. If excessive coughing and bronchoconstriction occurs, immediately administer an inhaled short-acting bronchodilator and other medical treatments as necessary.

11 DESCRIPTION

BRONCHITOL (mannitol) inhalation powder contains D-Mannitol (referred to throughout as mannitol) as the active ingredient. Mannitol is a hexahydric sugar alcohol, with the following chemical name hexane-1,2,3,4,5,6-hexol and chemical structure:

Mannitol is a white or almost white crystalline powder or free-flowing granules with an empirical formula of C6H14O6 and molecular weight of 182.2. Mannitol is freely soluble in water, and very slightly soluble in alcohol. Mannitol shows polymorphism.

BRONCHITOL contains mannitol powder spray dried into particles of respirable size filled into clear, colorless hard gelatin capsules. There are no inactive ingredients in BRONCHITOL.

The accompanying white plastic inhaler is comprised of a mouthpiece, blue piercing buttons, capsule chamber, and a removable cap. A blister pack consists of 10 capsules, each containing 40 mg mannitol. After a capsule is placed in the

capsule chamber and pierced by firmly pressing and releasing the buttons on the side of the device, the powder within the capsule becomes exposed and ready for dispersion into the airstream generated by the patient upon inhalation through the mouthpiece. Under standardized in vitro test conditions, the inhaler delivers 32.2 mg of mannitol per inhalation when tested at a flow rate of 60 L/min for 2 seconds. The actual amount of drug delivered to the lungs will depend on patient factors, such as inspiratory flow profile.

12 CLINICAL PHARMACOLOGY

12.1 Mechanism of Action

The precise mechanism of action of BRONCHITOL in improving pulmonary function in cystic fibrosis patients is unknown.

12.2 Pharmacodynamics

The pharmacodynamics of mannitol are unknown.

12.3 Pharmacokinetics

Absorption

Following oral inhalation of 635 mg, the mean mannitol peak plasma concentration (Cmax) was 13.71 mcg/mL while the mean extent of systemic exposure (AUC) was 73.15 mcg•hr/mL. The mean time to peak plasma concentration (Tmax) after oral inhalation was 1.5 hour.

Distribution

Based on intravenous administration, the volume of distribution of mannitol was 34.3 L.

Elimination

Metabolism

Mannitol is metabolized in a CYP-independent manner through the glycolytic pathway via dehydrogenation to fructose. The extent of metabolism of mannitol appears to be small. This is evident from a urinary excretion of about 87% of unchanged drug after an intravenous dose to healthy patients.

Excretion

Following oral inhalation, the elimination half-life of mannitol was 4.7 hours. The mean terminal elimination half-life for mannitol in plasma remained unchanged regardless of the route of administration (oral, inhalation, and intravenous). The urinary excretion rate versus time profile for mannitol was consistent for all routes of administration. The total clearance after intravenous administration was 5.1 L/hr while the renal clearance was 4.4 L/hr. Therefore, the clearance of mannitol was predominately via the kidney. Following inhalation of 635 mg of mannitol in 18 healthy patients, about 55% of the total dose was excreted in the urine as unchanged mannitol. Following oral or intravenous administration of a 500 mg dose, the corresponding values were 54% and 87% of the dose, respectively.

Specific Populations

Patients with Hepatic and Renal Impairment: Formal pharmacokinetic studies using BRONCHITOL have not been conducted in patients with hepatic or renal impairment. Since the drug is eliminated primarily via the kidney, an increase in systemic exposure can be expected in renally impaired patients.

Drug Interaction Studies

No formal drug interaction studies have been conducted with BRONCHITOL.

13 NONCLINICAL TOXICOLOGY

13.1 Carcinogenesis, Mutagenesis, Impairment of Fertility

Carcinogenesis

In 2-year carcinogenicity studies in rats and mice mannitol did not show evidence of carcinogenicity at oral dietary concentrations up to 5% (or 7,500 mg/kg on a mg/kg basis). These doses were approximately 55 and 30 times the

MRHDID, respectively, on a mg/m^2 basis.

Mutagenesis

Mannitol tested negative in the following assays: bacterial gene mutation assay, in vitro mouse lymphoma assay, in vitro chromosomal aberration assay in WI-38 human cells, in vivo chromosomal aberration assay in rat bone marrow, in vivo dominant lethal assay in rats, and in vivo mouse micronucleus assay.

Impairment of Fertility

The effect of inhaled mannitol on fertility has not been investigated.

14 CLINICAL STUDIES

 | Control (N=214) | BRONCHITOL (N=209)
Adjusted mean change from baseline | 12 mL | 63 mL
Adjusted mean difference (95% CI), p-value | 51 mL (6 to 97 mL), p=0.028

intention-to-treat population of adults of 78 mL (95% CI: 2 to 153 mL).

16 HOW SUPPLIED/STORAGE AND HANDLING

BRONCHITOL (mannitol) inhalation powder:

- 40 mg of mannitol per capsule
- capsules are clear, colorless and imprinted in black with “PXS” on cap and “40 mg” on body
- supplied in cartons containing 10, 140 or 560 capsules in blister packs co-packaged with 1, 1, and 4 inhalers respectively in a carton

BRONCHITOL is provided in 3 commercial presentations:

Pack Quantities | Inhalers | Capsules | NDC Number
4-week Treatment Pack (4 x 7-day treatment packs) | 4 | 560 | 84639-212-56
7-day Treatment Pack | 1 | 140 | 84639-212-14
Bronchitol Tolerance Test | 1 | 10 | 84639-212-04

BRONCHITOL should be stored between 68°F-77°F (20°C-25°C) with excursions permitted between 59°F-86°F (15°C- 30°C). [See USP Controlled Room Temperature]. Do not refrigerate. Do not freeze.

BRONCHITOL should only be used with the provided inhaler, which is a white plastic inhaler comprised of a mouthpiece, blue piercing buttons, capsule chamber, and a removable cap. All remaining unused (opened and unopened) blister packs and the inhalers should be properly discarded. Be sure to read the accompanying BRONCHITOL instructions completely before administration. If you have any questions, contact the supplier at 1-888-276-2144.

17 PATIENT COUNSELING INFORMATION

Advise the patient to read the FDA-approved patient labeling (Patient Information and Patient Instructions for Use).

BRONCHITOL Tolerance Test

Inform patients that a BRONCHITOL Tolerance Test is required prior to beginning treatment with BRONCHITOL. The

BRONCHITOL Tolerance Test must be performed by a healthcare practitioner equipped to monitor oxygen saturation (SpO2), perform spirometry (FEV1), and manage acute bronchospasm.

Inhaled Short-Acting Bronchodilator Use

Instruct patients that an inhaled short-acting bronchodilator such as albuterol must always be administered 5 to 15 minutes prior to every dose of BRONCHITOL.

Bronchospasm

Prior to administration, inform patients that bronchospasm can occur with inhalation of BRONCHITOL. If patient experiences bronchospasm, instruct the patient to discontinue BRONCHITOL and contact their healthcare practitioner right away.

Hemoptysis

Inform patients that hemoptysis can occur with inhalation of BRONCHITOL. If a patient experiences hemoptysis, instruct patients to discontinue BRONCHITOL and contact their healthcare practitioner right away.

Administration

Instruct patients on the proper administration of BRONCHITOL with the inhaler. The recommended dosage is 10 capsules (400 mg) twice a day. This requires inhaling the contents of 10 capsules administered individually once in the morning and once at least 2-3 hours before bed.

Manufactured by:

Arna Pharma Pty Ltd.

20 Rodborough Rd Frenchs Forest NSW 2086 AUSTRALIA

Manufactured for:

Pharmaxis Europe Limited

108 Q House Furze Road,

Sandyford Dublin 18,

D18AY29 Ireland

BRONCHITOL® is a registered trademark of Pharmaxis Europe Limited.

PATIENT INSTRUCTIONS FOR USE

BRONCHITOL® (mannitol) inhalation powder for oral inhalation use

This Patient Instructions for Use contains information on how to take BRONCHITOL.

Each BRONCHITOL box contains:

7-day Treatment Pack | 4-week Treatment Pack
- 140 Capsules (14 blister packs) | - 560 Capsules (56 blister packs)
- 1 Inhaler | - 4 Inhalers
- Prescribing Information | - Prescribing Information

Important Information You Need to Know Before Using BRONCHITOL

- Do not use BRONCHITOL until your healthcare provider has performed the BRONCHITOL Tolerance Test (BTT) and approved you for treatment. This is to make sure you get the right treatment if you have a severe reaction.
- For oral inhalation only
- Do not swallow BRONCHITOL capsules.
- Use an inhaled short-acting bronchodilator 5 to15 minutes before every dose of BRONCHITOL.
- Use BRONCHITOL 2 times each day. Inhale through your mouth (oral inhalation) the capsule contents in 10 single BRONCHITOL capsules:
  - 1 time in the morning
  - 1 time at least 2 to 3 hours before bedtime

Preparing to use BRONCHITOL

BRONCHITOL is supplied to people in cartons containing 140 or 560 capsules in blister packs. Supplies you will need to use BRONCHITOL:

- 1 Blister pack
- 1 Inhaler
- Bronchodilator (and spacer for bronchodilator if needed)
- Sink or hand washing station

Before using BRONCHITOL:

Use an inhaled bronchodilator 5 to15 minutes before using BRONCHITOL (See Figure A).

Clean and dry hands well (See Figure B).

Inhaler use steps for inhalation of the contents of a single capsule: Step 1. Remove cap (See Figure C).

Step 2. Twist open inhaler by turning the mouthpiece to the right. (See Figure D).

Step 3. Take 1 capsule out of the blister pack and put it in the chamber. (See Figure E).

Do not place capsule into the mouthpiece of the inhaler.

Step 4. Hold inhaler upright and turn the mouthpiece to the left until it locks in place. (See Figure F).

Step 5. Push both piercing buttons at the same time. Release both piercing buttons at the same time (See Figure G).

Keep inhaler upright. Never keep piercing buttons pressed.

Step 6. Breathe out (exhale) fully (See Figure H).

Do not breathe out into inhaler.

Step 7. Close lips around the mouthpiece and take a steady deep breath in through your mouth. Do not breathe through your nose. Remove inhaler from mouth. Hold breath for 5 seconds before exhaling, do not breathe out (exhale) into inhaler (See Figure I).

You should hear a rattling sound while breathing in. If you do not, tap bottom of inhaler firmly and repeat steps 6 and 7.

Step 8. Open the inhaler by turning the cap to the right. If powder is left in capsule, repeat steps 6 and 7. After the capsule is empty, throw away. (See Figure J).

Step 9. Repeat steps 3 to 8 for all 10 capsules in 1 blister pack (See Figure K).

Breathe in (inhale) contents of each capsule one after another until all 10 capsules in the blister pack are used.

Step 10. After inhaling contents of all 10 capsules, close mouthpiece and place cap on inhaler (See Figure L).

Step 11. Continue using BRONCHITOL for 7 days then throw away (discard) the inhaler (See Figure M).

How should I store BRONCHITOL?

- Store BRONCHITOL at room temperature between 68°F to77°F (20°C to 25°C).
- If your BRONCHITOL capsules are stored at temperatures more than 86°F (30°C), throw them away.
- Do not freeze BRONCHITOL.
- Do not refrigerate BRONCHITOL.
- Keep BRONCHITOL and all medicines out of the reach of children.

Cleaning your BRONCHITOL inhaler.

- Your inhaler should give you the correct dose of medicine for 7 days without needing cleaning. However, if your inhaler does need cleaning:
  - Make sure your inhaler is empty.
  - Wash your inhaler in warm water with the mouthpiece open.
  - Shake it until there are no large water droplets left in the inhaler.
  - Leave it to dry in the air by laying it on its side with the mouthpiece open.
  - Allow the inhaler to dry fully (or completely) after it has been washed.

Caring for your BRONCHITOL inhaler.

- Keep your inhaler dry and always make sure your hands are completely dry before using it.
- Do not breathe or cough into your inhaler.
- Do not take your inhaler apart.
- Do not place a capsule directly into the mouthpiece of your inhaler.
- Do not leave a used capsule in your inhaler chamber.
- Use a new inhaler after 7 days.
- If your inhaler breaks, call to your healthcare provider.

For more information about BRONCHITOL or how to use your inhaler, call 1-888-276-2144.

Manufactured by:

Arna Pharma Pty Ltd.

20 Rodborough Road

Frenchs Forest NSW

2086 AUSTRALIA

Manufactured for:

Pharmaxis Europe Limited

108 Q House Furze Road,

Sandyford Dublin 18,

D18AY29 Ireland

1-888-276-2144

BRONCHITOL is registered in the US Patent and Trademark Office.

This Patient Instructions for Use has been approved by the U.S. Food and Drug Administration.

Revised: 06/2024

Principle Display Panel - 40 mg 4 Week Carton

Principal Display Panel - 40 mg 4 Week Carton Label

Rx Only

NDC 84639-212-56

Caution: Federal Law Prohibits Dispensing Without A Prescription

Bronchitol®

(mannitol) inhalation powder

40 mg per capsule

FOR ORAL INHALATION ONLY

Do Not Swallow Bronchitol Capsules

Complete entire package (56 Blister Packs) for 28 days treatment

Contents:

56 Blister Cards: 560 capsules (40 mg each)

4 Bronchitol devices: For use with enclosed capsules only

See package insert for complete dosage information

For more information, call 1-888-661-9260.

Principal Display Panel - 40 mg 7 Day Carton Label

Rx Only

NDC 84639-212-14

Bronchitol®

(mannitol) inhalation powder

40 mg per capsule

FOR ORAL INHALATION ONLY

Do Not Swallow Bronchitol Capsules

Complete entire package (14 Blister Packs) for 7 days treatment

Contents:

- 14 Blister Packs: 140 capsules (40 mg each)
- 1 Bronchitol inhaler: For use with enclosed capsules only
- Quick reference guide
- Package Insert

See package insert for complete dosage information

For more information, call 1-888-276-0618.

Principal Display Panel - 40 mg Tolerance Test Carton Label

Rx Only

NDC 84639-212-04

Bronchitol®

(mannitol) inhalation powder

Tolerance Test

40 mg per capsule

FOR ORAL INHALATION ONLY

Contents:

- 1 Blister Pack: 10 capsules
- 1 Bronchitol inhaler:

For use with enclosed capsules only

- Tolerance Test Instructions
- Package Insert

The Bronchitol Tolerance Test MUST be completed to
identify bronchial hyperresponsiveness to mannitol
prior to prescribing Bronchitol. Read Tolerance Test
instructions for detailed procedure.

Do Not Swallow Bronchitol Capsules